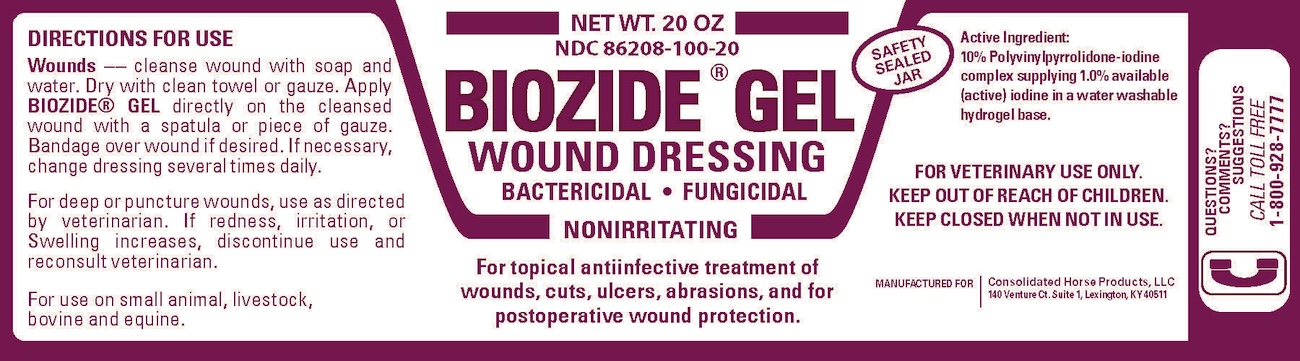 DRUG LABEL: Biozide
NDC: 86208-100 | Form: GEL
Manufacturer: Consolidated Horse Products
Category: animal | Type: OTC ANIMAL DRUG LABEL
Date: 20250812

ACTIVE INGREDIENTS: POVIDONE-IODINE 10 g/100 g
INACTIVE INGREDIENTS: WATER

Biozide

INDICATIONS AND USAGE

DIRECTIONS FOR USE:
Wounds -- cleanse wound with soap and water. Dry with clean towel or gauze. Apply BIOZIDE GEL directly on the cleansed wound with a spatula or piece of gauze. Bandage over wound if desired. If necessary, change dressing several times daily.

For deep or puncture wounds, use as directed by veterinarian. If redness, irritation, or swelling increases, discontinue use and reconsult veterinarian.

For use on small animal, livestock, bovine and equine.

Active Ingredient:
10% polvinylpyrrolidone-iodine complex supplying 1.0% available (active) iodine in a water washable hydrogel base.

FOR VETERINARY USE ONLY.
KEEP OUT OF REACH OF CHILDREN.
KEEP CLOSED WHEN NOT IN USE.

MANUFACTURED FOR: Consolidated Horse Products, LLC, 140 Venture Ct., Suite 1, Lexington, Ky 40511

QUESTIONS? COMMENTS ? SUGGESTIONS?
CALL TOLL FREE
1-800-928-7777

BIOZIDE GEL 20 0Z (86208-100-20)

NET WT. 20 OZ
NDC: 86208-100-20

BIOZIDE GEL

WOUND DRESSING

BACTERICIDAL FUNGICIDAL
NONIRRITATING

For topical antiinfective treatment of wounds, cuts, ulcers, abrasions, and for postoperative wound protection.